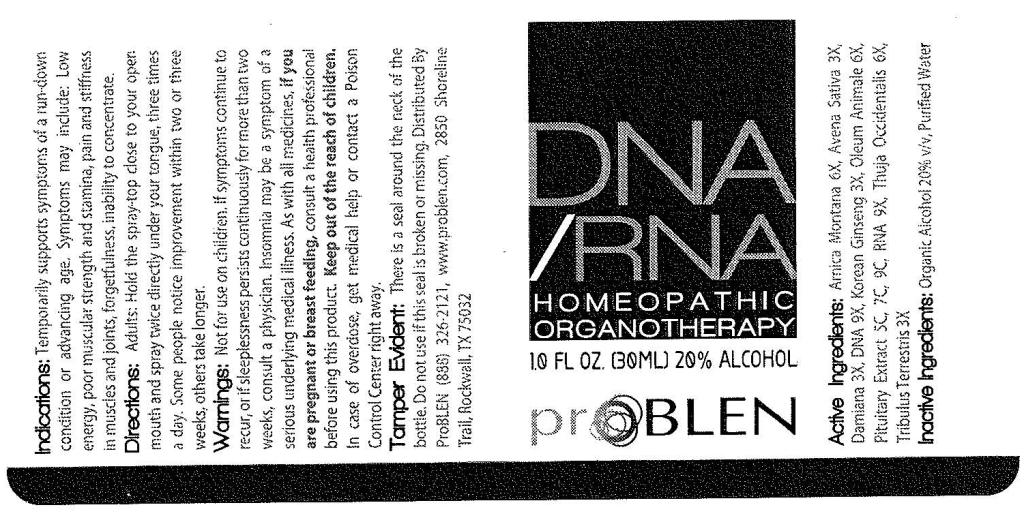 DRUG LABEL: ProBlen DNA RNA Rejuvenation
NDC: 50845-0132 | Form: SPRAY
Manufacturer: Liddell Laboratories, Inc.
Category: homeopathic | Type: HUMAN OTC DRUG LABEL
Date: 20120206

ACTIVE INGREDIENTS: ARNICA MONTANA 6 [hp_X]/1 mL; AVENA SATIVA FLOWERING TOP 3 [hp_X]/1 mL; TURNERA DIFFUSA LEAFY TWIG 3 [hp_X]/1 mL; ASIAN GINSENG 3 [hp_X]/1 mL; THUJA OCCIDENTALIS LEAFY TWIG 6 [hp_X]/1 mL; HERRING SPERM DNA 9 [hp_X]/1 mL; SACCHAROMYCES CEREVISIAE RNA 9 [hp_X]/1 mL; TRIBULUS TERRESTRIS ROOT 3 [hp_X]/1 mL; CERVUS ELAPHUS HORN OIL 6 [hp_X]/1 mL; BOS TAURUS PITUITARY GLAND 5 [hp_C]/1 mL
INACTIVE INGREDIENTS: WATER; ALCOHOL

ProBLEN DNA RNA Rejuvenation

ACTIVE INGREDIENT

ACTIVE INGREDIENTS: Arnica montana 6X, Avena sativa 3X, Damiana 3X, DNA 9X, Korean ginseng 3X, Oleum animale 6X, Pituitary bovinum 5C, 7C, 9C, RNA 9X, Thuja occidentalis 6X, Tribulus terrestris 3X.

PURPOSE

INDICATIONS: Temporarily supports symptoms of a run-down condition or advancing age. Symptoms may include: Low energy, poor muscular strength and stamina, pain and stiffness in muscles and joints, forgetfulness, inability to concentrate.

WARNINGS

WARNINGS: Not for use on children. If symptoms continue to recur, or if sleeplessness persists continuously for more than two weeks, consult a physician. Insomnia may be a symptom of a serious underlying medical illness.

As with all medicines, if you are pregnant or breast feeding, consult a health professional before using this product.

Keep out of the reach of children. In case of overdose, get medical help or contact a Poison Control Center right away.

TAMPER EVIDENT: There is a seal around the neck of the bottle. Do not use if this seal is broken or missing.

DOSAGE AND ADMINISTRATION

DIRECTIONS: Adults: Hold the spray-top close to your open mouth and spray twice directly under your tongue, three times a day. Some people notice improvement within two or three weeks, others take longer.

INACTIVE INGREDIENT

INACTIVE INGREDIENTS: Organic alcohol 20% v/v, Purified water.

KEEP OUT OF REACH OF CHILDREN

KEEP OUT OF THE REACH OF CHILDREN. In case of overdose, get medical help or contact a Poison Control Center right away.

INDICATIONS AND USAGE

INDICATIONS: Temporarily supports symptoms of a run-down condition or advancing age. Symptoms may include: Low energy, poor muscular strength and stamina, pain and stiffness in muscles and joints, forgetfulness, inability to concentrate.

QUESTIONS

Distributed By:

ProBLEN

2850 Shoreline Trail

Rockwall, TX 75032

(888) 326-2121

www.problen.com

PACKAGE LABEL

DNA RNA

HOMEOPATHIC ORGANOTHERAPY

1.0 FL OZ (30 ML)

proBLEN